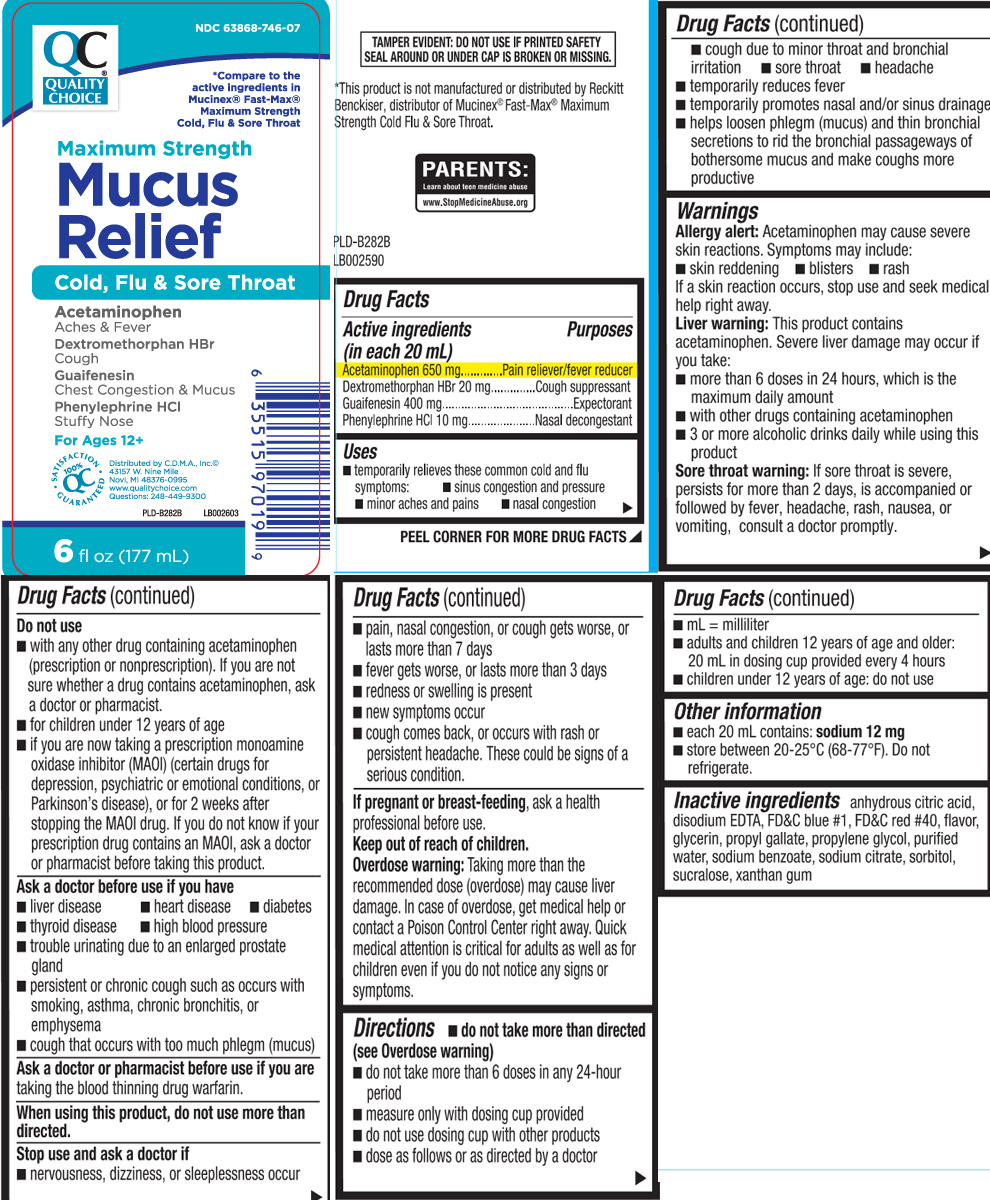 DRUG LABEL: Mucus Relief Cold Flu and Sore Throat
NDC: 63868-746 | Form: LIQUID
Manufacturer: QUALITY CHOICE (Chain Drug Marketing Association)
Category: otc | Type: HUMAN OTC DRUG LABEL
Date: 20240501

ACTIVE INGREDIENTS: ACETAMINOPHEN 650 mg/20 mL; DEXTROMETHORPHAN HYDROBROMIDE 20 mg/20 mL; GUAIFENESIN 400 mg/20 mL; PHENYLEPHRINE HYDROCHLORIDE 10 mg/20 mL
INACTIVE INGREDIENTS: ANHYDROUS CITRIC ACID; DISODIUM EDTA-COPPER; FD&C BLUE NO. 1; FD&C RED NO. 40; GLYCERIN; PROPYL GALLATE; PROPYLENE GLYCOL; WATER; SODIUM BENZOATE; TRISODIUM CITRATE DIHYDRATE; SORBITOL; SUCRALOSE; XANTHAN GUM

Drug Facts

Active ingredients (in each 20 mL)

Acetaminophen 650 mg

Dextromethorphan HBr 20 mg

Guaifenesin 400 mg

Phenylephrine HCl 10 mg

Purposes

Pain reliever/fever reducer

Cough suppressant

Expectorant

Nasal decongestant

Uses

- temporarily relieves these common cold and flu symptoms:
  - sinus congestion and pressure
  - minor aches and pains
  - nasal congestion
  - cough due to minor throat and bronchial irritation
  - sore throat
  - headache
- temporarily reduces fever
- temporarily promotes nasal and/or sinus drainage
- helps loosen phlegm (mucus) amd thin bronchial secretions to rid the bronchial passageways of bothersome mucus and make coughs more productive

Warnings

Allergy alert: Acetaminophen may cause severe skin reactions. Symptoms may include:

- skin reddening
- blisters
- rash

If a skin reaction occurs, stop use and seek medical help right away.

Liver warning: This product contains acetaminophen. Severe liver damage may occur if you take:

- more than 6 doses in 24 hours, which is the maximum daily amount
- with other drugs containing acetaminophen
- 3 or more alcoholic drinks everyday while using this product

Sore throat warning: If sore throat is severe, persists for more than 2 days, is accompanied or followed by fever, headache, rash, nausea or vomiting, consult a doctor promptly.

Do not use

- for children under 12 years of age
- if you are now taking a prescription monoamine oxidase inhibitor (MAOI) (certain drugs for depression, psychiatric or emotional conditions, or Parkinson's disease), or for 2 weeks after stopping the MAOI drug. If you do not know if your prescription drug contains an MAOI, ask a doctor or pharmacist before taking this product.
- with any other drug containing acetaminophen (prescription or nonprescription). If you are not sure whether a drug contains acetaminophen, ask a doctor or pharmacist.

Ask a doctor before use if you have

- diabetes
- liver disease
- heart disease
- thyroid disease
- high blood pressure
- persistent or chronic cough such as occurs with smoking, asthma, chronic bronchitis or emphysema
- cough that occurs with too much phlegm (mucus)
- trouble urinating due to an enlarged prostate gland

Ask a doctor or pharmacist before use if you are

taking the blood thinning drug warfarin.

When using this product,

do not use more than directed.

Stop use and ask a doctor if

- redness or swelling is present
- nervousness, dizziness or sleeplessness occur
- new symptoms occur
- pain, nasal congestion or cough gets worse or lasts more than 7 days
- fever gets worse or lasts more than 3 days
- cough comes back, or occurs with rash or persistent headache

These could be signs of a serious condition.

If pregnant or breast-feeding,

ask a health professional before use.

Keep out of reach of children.

Overdose warning: Taking more than the recommended dose (overdose) may cause liver damage. In case of overdose, get medical help or contact a Poison Control Center (1-800-222-1222) right away. Quick medical attention is critical for adults as well as for children even if you do not notice any signs or symptoms.

Directions

- do not take more than directed (see Overdose warning)
- do not take more than 6 doses in any 24-hour period
- measure only with dosing cup provided
- do not use dosing cup with other products
- dose as follows or as directed by a doctor
- mL=milliliter
- adults and children 12 years of age and older: 20 mL in dosing cup provided every 4 hours
- children under 12 years of age: do not use

Other information

- each 20 mL contains: sodium 12 mg
- store at 20º-25ºC (68º-77ºF). Do not refrigerate.

Inactive ingredients

anhydrous citric acid, disodium EDTA, FD&C blue #1, FD&C red #40, glycerin, natural & artificial flavor, propyl gallate, propylene glycol, purified water, sodium benzoate, sodium citrate, sorbitol, sucralose, xanthan gum

Principal Display Panel

*Compare to the active ingredients in Mucinex® Fast-Max® Maximum Strength Cold, Flu & Sore Throat

Maximum Strength

Mucus Relief

Cold, Flu & Sore Throat

Acetaminophen

Aches & fever

Dextromethorphan HBr

Cough

Guaifenesin

Chest congestion and mucus

Phenylephrine HCl

Stuffy nose

For ages 12+

Distributed by CDMA Inc.

43157 W. Nine Mile

novi, MI 48376-0995

qualitychoice.com

Questions: 248-449-9300

FL OZ (mL)

TAMPER EVIDENT: DO NOT USE IF PRINTED SAFETY SEAL AROUND OR UNDER CAP IS BROKEN OR MISSING

*This product is not manufactured or distributed by Reckitt Benckiser, distributor of Mucinex® Fast-Max® maximum Strength Cold Flu & Sore Throat

Package Label

Quality Choice Maximum Strength Mucus Relief Cold, Flu & Sore Throat